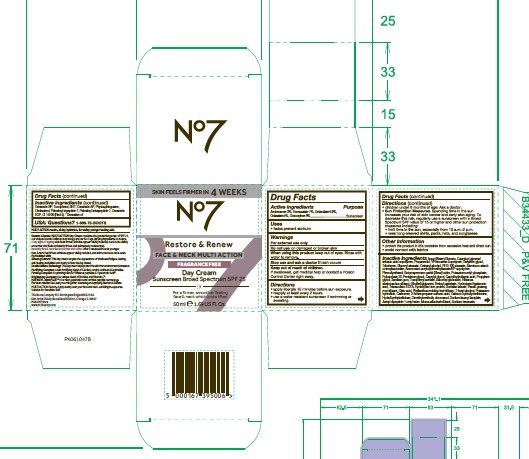 DRUG LABEL: No 7 Restore and Renew Multi Action Fragrance Free Day Cream SPF 25
NDC: 61589-9102 | Form: CREAM
Manufacturer: BCM Cosmetique SAS
Category: otc | Type: HUMAN OTC DRUG LABEL
Date: 20251205

ACTIVE INGREDIENTS: AVOBENZONE 3 g/50 g; OCTISALATE 5 g/50 g; OCTOCRYLENE 9 g/50 g; OCTINOXATE 0.8 g/50 g; HOMOSALATE 7 g/50 g
INACTIVE INGREDIENTS: SODIUM LAUROYL LACTYLATE; MORUS ALBA LEAF; CAPRYLOYL GLYCERIN/SEBACIC ACID COPOLYMER (2000 MPA.S); PROPANEDIOL; TERT-BUTYL ALCOHOL; 3-AMINOPROPANE SULFONIC ACID; CAPRYLYL GLYCOL; SODIUM HYALURONATE; PALMITOYL TETRAPEPTIDE-7; CERAMIDE 3; CHOLESTEROL; ACETYL TYROSYLARGININE CETYL ESTER; PHYTOSPHINGOSINE; HYDROXYETHYL CELLULOSE (100 MPA.S AT 2%); GLYCERYL STEARATE SE; ALUMINUM STARCH OCTENYLSUCCINATE; PALMITOYL TRIPEPTIDE-1; CETEARYL ALCOHOL; CALCIUM HYDROXYMETHIONINE; CI 14700; POLYSORBATE 20; GLYCERIN; TRIBEHENIN; POTASSIUM CETYL PHOSPHATE; BUTYLENE GLYCOL; PHYLLANTHUS EMBLICA FRUIT; VITAMIN A PALMITATE; CAPRYLHYDROXAMIC ACID; HYDROLYZED RICE PROTEIN (ENZYMATIC; 2000 MW); DIMETHYLMETHOXY CHROMANOL; CARBOMER; ALPHA-TOCOPHEROL ACETATE; ASCORBYL GLUCOSIDE; VINYLPYRROLIDONE/EICOSENE COPOLYMER; PEG-100 STEARATE; TETRASODIUM EDTA; POTASSIUM HYDROXIDE; ETHYLHEXYLGLYCERIN; PROPYLENE GLYCOL; CERAMIDE 1; PENTYLENE GLYCOL; WATER; AMMONIUM ACRYLOYLDIMETHYLTAURATE/VP COPOLYMER; BHT; BUTYROSPERMUM PARKII (SHEA) BUTTER; SORBITAN MONOLAURATE; XANTHAN GUM; PANAX GINSENG ROOT; TOCOPHEROL; ABELMOSCHUS MOSCHATUS WHOLE; CITRIC ACID; SODIUM BENZOATE; CERAMIDE 6 II; PHENOXYETHANOL

No 7 Restore & Renew Multi Action Fragrance Free Day Cream SPF 25

Warnings

For extenal use only

Do not use on damaged of broken skin

When using this product keep out of eyes. Rinse with water to remove.

Stop use and ask a doctor if rash occurs.

Keep out of reach of children.

If swallowed, get medical help or contact a Poison Control Center right away.

Active Ingredients

Avobenzone 3%

Homosalate 7%

Octinoxate 0.8%

Octisalate 5%

Octocrylene 9%

Inactive Ingredients

Aqua (Water),Glycerin, Capryloyl glycerin/
sebacic acid copolymer, Propanediol, VP/eicosene copolymer, Butylene glycol,
Tribehenin, Glyceryl stearate, Cetearyl alcohol, PEG-100 stearate, Aluminum starch
octenylsuccinate, Ammonium acryloyldimethyltaurate/VP copolymer,
Phenoxyethanol, Butyrospermum parkii (Shea) butter, Potassium cetyl phosphate,
Polysorbate 20, Pentylene glycol, Caprylyl glycol, Caprylhydroxamic acid, Propylene
glycol, Xanthan gum, Tocopheryl acetate, Ascorbyl glucoside, Hibiscus
abelmoschus extract, Ethylhexylglycerin, Retinyl palmitate, Hydrolyzed hyaluronic
acid, Tetrasodium EDTA, Hydrolyzed rice protein, Sorbitan laurate, Panax ginseng
root extract, Citric acid, Phyllanthus emblica fruit extract, T-butyl alcohol, Potassium
hydroxide, Carbomer, 3-Aminopropane sulfonic acid, Calcium hydroxymethionine,
Hydroxyethylcellulose, Dimethylmethoxy chromanol, Sodium lauroyl lactylate,
Acetyl dipeptide-1 cetyl ester, Morus alba leaf extract, Sodium benzoate,CeramidCeramide NP, Tocopherol, BHT,

Ceramide AP, Phytosphingosine, Cholesterol, Palmitoyl tripeptide-1, Palmitoyl tetrapeptide-7, Ceramide EOP,

CI 14700 (Red 4) *Derivative of

Uses

Helps prevent sunburn

Directions

Apply liberally 15 minutes before sun exposure.

Reapply at least every 2 hours.

Use a water resistant sunscreen if swimming or sweating.

Children under 6 months of age: Ask a doctor.

Sun Protection Measures

Spending time in the sun increases your risk of skin cancer and early skin aging. To decrease this risk, regularly use a sunscreen with a Broad Spectrum SPF value of 15 or higher and other sun protection measures including:

Limit time in the sun, especially from 10 a.m. - 2 p.m.

Wear long-sleeved shirts, pants, hats, and sunglasses

STORAGE AND HANDLING

Protect the product in this container from excessive heat and direct sun

Avoid contact with fabrics

Questions? 1-866-75-BOOTS

Active Ingredients Purpose

Avobenzone 3% Sunscreen

Homosalate 7% Sunscreen

Octinoxate 0.8% Sunscreen

Octisalate 5% Sunscreen

Octocrylene 9% Sunscrren

Warning

For external use only

Do not use on damaged or broken skin

When using this product keep out of eyes. Rinse with water to remove.

Stop use and ask a doctor if rash occurs.

Keep Out of Reach of Children.

If swallowed, get medical help or contact a Poison Control Center right away.

Directions

- apply liberally 15 minutes before sun exposure
- reapply at least every 2 hours
- use a water resistant sunscreen if swimming or sweating
- children under 6 months of age. Ask a doctor
- Sun Protection Measures. Spending time in the sun increases your risk of skin cancer and early skin aging. To decrease this risk, regularly use a sunscreen with a Broad Spectrum SPF value of 15 or higherand other sun protection measures including:
- limit time in the sun, especially from 10 a.m. - 2 p.m.
- wear long-sleeved shirts, pants, hats, and sunglasess